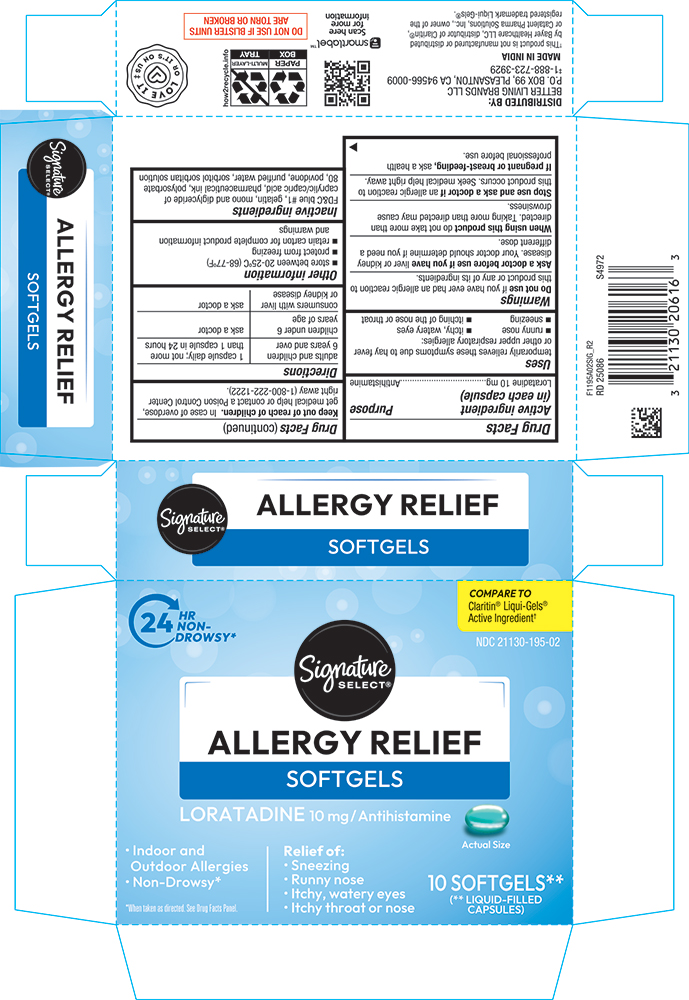 DRUG LABEL: Allergy Relief
NDC: 21130-195 | Form: CAPSULE, LIQUID FILLED
Manufacturer: Safeway
Category: otc | Type: HUMAN OTC DRUG LABEL
Date: 20250430

ACTIVE INGREDIENTS: LORATADINE 10 mg/1 1
INACTIVE INGREDIENTS: GELATIN; CAPRIC ACID; POVIDONE K30; WATER; SORBITOL; POLYSORBATE 80; SORBITAN; FD&C BLUE NO. 1

SIG - 1195A - 2025-0430

Drug Facts

Active Ingredient (in each capsule)

Loratadine 10mg

Purpose

Antihistamine

Uses

temporarily relieves these symptoms due to hay fever or other upper respiratory allergies

• runny nose

• sneezing

• itchy, water eyes

• itching of the nose or throat

Warnings

Do not useif you have ever had an allergic reaction to this product or any of its ingredients.

Ask a doctor before use if you haveliver or kidney disease. Your doctor should determine if you need a different dose.

WHEN USING

When using this productdo not take more than directed. Taking more than directed may cause drowsiness.

Stop use and ask a doctor if an allergic reaction to this product occurs. Seek medical help right away

PREGNANCY OR BREAST FEEDING

If pregnant or breast-feeding, ask a health professional before use.

Keep out of reach of children. In case of overdose, get medical help or contact a Poison Control Center right away (1-800-222-1222).

Directions

adults and children 6 years and over | 1 capsule daily; not more than 1 capsule in 24 hours
children under 6 years of age | ask a doctor
consumers with liver or kidney disease | ask a doctor

Other information

• Store between 20-25˚C (68-77˚F)

• protect from freezing

• retain carton for complete information and warnings

Inactive ingredients

FD&C Blue no. 1, gelatine, mono anddiglyceride of caprilic/capric acid, pharmaceutical ink, polysorbate 80,povidone, purified water, sorbitol, sorbitan solution.

PRINCIPAL DISPLAY PANEL

24 HR NON-DWOSY*

Compare to Claritin® Liqui-Gels® active ingredient†

NDC 21130-195-02

Signature Select®

ALLERGY RELIEF

SOFTGELS

LORATADINE 10mg / Antihistamine

Actual Size

Indoor and Outdoor Allergies

Non-Drowsy*

*When taken as directed. See Drug Facts Panel.

Relief of:

• Sneezing

• Runny Nose

• Itchy, Watery Eyes

• Itchy Throat or Nose

10 SOFTGELS**

(**LIQUID-FILLED CAPSULES)